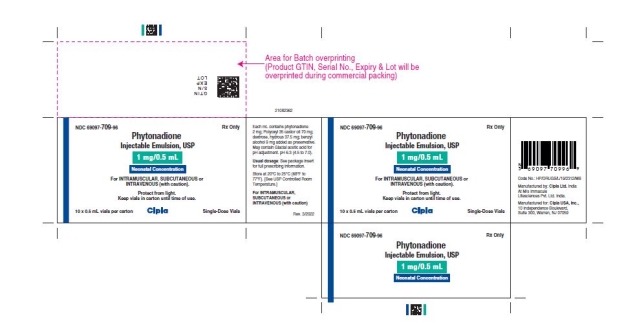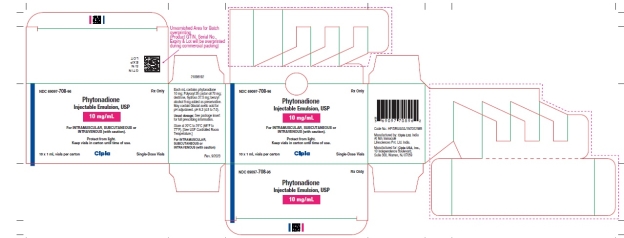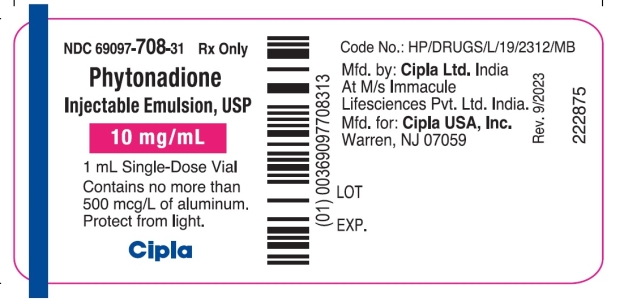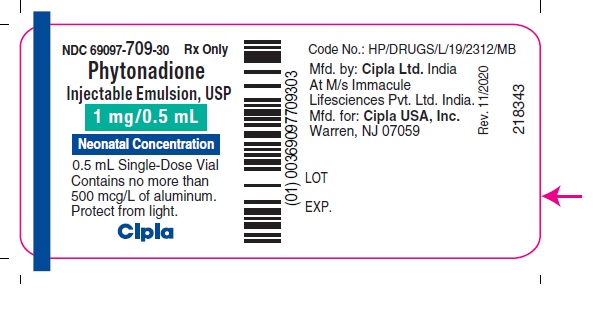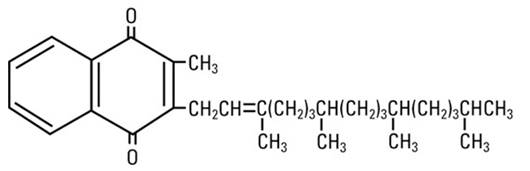 DRUG LABEL: Phytonadione
NDC: 69097-709 | Form: INJECTION, EMULSION
Manufacturer: Cipla USA Inc.
Category: prescription | Type: HUMAN PRESCRIPTION DRUG LABEL
Date: 20240712

ACTIVE INGREDIENTS: PHYTONADIONE 1 mg/0.5 mL
INACTIVE INGREDIENTS: POLYOXYL 35 CASTOR OIL; DEXTROSE MONOHYDRATE; BENZYL ALCOHOL; WATER; ACETIC ACID

HIGHLIGHTS OF PRESCRIBING INFORMATION

These highlights do not include all the information needed to use PHYTONADIONE INJECTABLE EMULSION safely and effectively. See full prescribing information for PHYTONADIONE INJECTABLE EMULSION.
PHYTONADIONE injectable emulsion, for intravenous, intramuscular, and subcutaneous use.
Initial U.S. Approval: 1960

WARNING-HYPERSENSITIVITY REACTIONS WITH INTRAVENOUS AND INTRAMUSCULAR USE

See full prescribing information for complete boxed warning.

Fatal hypersensitivity reactions, including anaphylaxis, have occurred during and immediately after INTRAVENOUS and INTRAMUSCULAR injection of phytonadione injectable emulsion. Reactions have occurred despite dilution to avoid rapid infusion and upon first and subsequent doses. Avoid the intravenous and intramuscular routes of administration unless the subcutaneous route is not feasible and the serious risk is justified. (5.1)

1 INDICATIONS AND USAGE

Phytonadione injectable emulsion is a vitamin K replacement indicated for the treatment of the following coagulation disorders which are due to faulty formation of factors II, VII, IX and X when caused by vitamin K deficiency or interference with vitamin K activity.

- Anticoagulant-induced hypoprothrombinemia deficiency caused by coumarin or indanedione derivatives; (1.1)
- Hypoprothrombinemia due to antibacterial therapy; (1.1)
- Hypoprothrombinemia secondary to factors limiting absorption or synthesis of vitamin K, e.g., obstructive jaundice, biliary fistula, sprue, ulcerative colitis, celiac disease, intestinal resection, cystic fibrosis of the pancreas, and regional enteritis; (1.1)
- Other drug-induced hypoprothrombinemia where is it definitely shown that the result is due to interference with vitamin K metabolism, e.g., salicylates. (1.1)

Phytonadione injectable emulsion is indicated for prophylaxis and treatment of vitamin K-deficiency bleeding in neonates. (1.2)

2 DOSAGE AND ADMINISTRATION

- Administer phytonadione injectable emulsion by the subcutaneous route, whenever possible. (2.1)
- When intravenous administration is unavoidable, inject the drug very slowly, not exceeding 1 mg per minute. (2.1)

3 DOSAGE FORMS AND STRENGTHS

Injection: 2 mg/mL and 10 mg/mL single-dose vials. (3)

4 CONTRAINDICATIONS

Hypersensitivity to any component of this medication. (4)

5 WARNINGS AND PRECAUTIONS

- Risk of Serious Adverse Reactions in Infants due to Benzyl Alcohol Preservative: Use benzyl alcohol-free formulations in neonates and infants, if available. (5.1)
- Cutaneous Reactions: May occur with parenteral use. Discontinue drug and manage medically. (5.3)

6 ADVERSE REACTIONS

Most common adverse reactions are cyanosis, diaphoresis, dizziness, dysgeusia, dyspnea, flushing, hypotension and tachycardia. (6)

To report SUSPECTED ADVERSE REACTIONS, contact Cipla Ltd at 1-866-604-3268, or FDA at 1-800-FDA-1088 or www.fda.gov/medwatch.

7 DRUG INTERACTIONS

Anticoagulants: May induce temporary resistance to prothrombin-depressing anticoagulants. (7)

8 USE IN SPECIFIC POPULATIONS

- Pregnancy: If available, use the preservative-free formulation in pregnant women. (8.1)
- Lactation: If available, use the preservative-free formulation in lactating women. (8.2)
- Pediatric Use: The safety and effectiveness of phytonadione injectable emulsion in pediatric patients from 6 months to 17 years have not been established. (8.4)

FULL PRESCRIBING INFORMATION

WARNING-HYPERSENSITIVITY REACTIONS WITH INTRAVENOUS AND INTRAMUSCULAR USE

Fatal hypersensitivity reactions, including anaphylaxis, have occurred during and immediately after intravenous and intramuscular injection of phytonadione injectable emulsion. Reactions have occurred despite dilution to avoid rapid intravenous infusion and upon first dose. Avoid the intravenous and intramuscular routes of administration unless the subcutaneous route is not feasible and the serious risk is justified [see Warnings and Precautions (5.1)].

1 INDICATIONS AND USAGE

1.1 Treatment of Hypoprothrombinemia Due to Vitamin K Deficiency or Interference

Phytonadione injectable emulsion is indicated for the treatment of the following coagulation disorders which are due to faulty formation of factors II, VII, IX and X when caused by vitamin K deficiency or interference with vitamin K activity:

- anticoagulant-induced hypoprothrombinemia caused by coumarin or indanedione derivatives;
- hypoprothrombinemia due to antibacterial therapy;
- hypoprothrombinemia secondary to factors limiting absorption or synthesis of vitamin K, e.g., obstructive jaundice, biliary fistula, sprue, ulcerative colitis, celiac disease, intestinal resection, cystic fibrosis of the pancreas, and regional enteritis;
- other drug-induced hypoprothrombinemia where it is definitely shown that the result is due to interference with vitamin K metabolism, e.g., salicylates.

1.2 Prophylaxis and Treatment of Vitamin K-Deficiency Bleeding in Neonates

Phytonadione injectable emulsion is indicated for prophylaxis and treatment of vitamin K-deficiency bleeding in neonates.

2 DOSAGE AND ADMINISTRATION

2.1 Dosing Considerations

Whenever possible, administer phytonadione injectable emulsion by the subcutaneous route [see Boxed Warning]. When intravenous administration is unavoidable, inject the drug very slowly, not exceeding 1 mg per minute [see Warnings and Precautions (5.1)].

Monitor international normalized ratio (INR) regularly and as clinical conditions indicate. Use the lowest effective dose of phytonadione injectable emulsion.

The coagulant effects of phytonadione injectable emulsion are not immediate; improvement of INR may take 1-8 hours. Interim use of whole blood or component therapy may also be necessary if bleeding is severe.

Whenever possible, administer benzyl alcohol-free formulations in pediatric patients [see Warnings and Precautions (5.2), Use in Specific Populations (8.4)].

When phytonadione injectable emulsion is used to correct excessive anticoagulant-induced hypoprothrombinemia, anticoagulant therapy still being indicated, the patient is again faced with the clotting hazards existing prior to starting the anticoagulant therapy. Phytonadione is not a clotting agent, but overzealous therapy with phytonadione injectable emulsion may restore conditions which originally permitted thromboembolic phenomena. Dosage should be kept as low as possible, and INR should be checked regularly as clinical conditions indicate.

2.2 Recommended Dosage for Coagulation Disorders from Vitamin K Deficiency or Interference

The recommended dosage of phytonadione injectable emulsion is based on whether the hypoprothrombinemia is anticoagulant-induced (e.g., due to coumarin or indanedione derivatives) or non-anticoagulant-induced (e.g., due to antibiotics; salicylates or other drugs; factors limiting absorption or synthesis) as follows:

- Anticoagulant-Induced Hypoprothrombinemia: Phytonadione injectable emulsion 2.5 mg to 10 mg or more subcutaneously, intramuscularly, or intravenously. Up to 25 mg to 50 mg may be administered as a single dose.

Repeated large doses of phytonadione injectable emulsion are not warranted in liver disease if the initial response is unsatisfactory. Failure to respond to phytonadione injectable emulsion may indicate that the condition being treated is inherently unresponsive to phytonadione injectable emulsion.

- Hypoprothrombinemia Due to Other Causes (Non-Anticoagulation-Induced Hypoprothrombinemia): Phytonadione injectable emulsion 2.5 mg to 25 mg or more intravenously, intramuscularly, or subcutaneously. Up to 50 mg may be administered as a single dose.

Evaluate INR after 6-8 hours, and repeat dose if INR remains prolonged. Modify subsequent dosage (amount and frequency) based on the INR or clinical condition.

2.3 Recommended Dosage for Prophylaxis and Treatment of Vitamin K Deficiency Bleeding in Neonates

Prophylaxis of Vitamin K-Deficiency Bleeding in Neonates

The recommended dosage of phytonadione injectable emulsion is 0.5 mg to 1 mg within one hour of birth for a single dose.

Treatment of Vitamin K Deficiency Bleeding in Neonates

The recommended dosage of phytonadione injectable emulsion is 1 mg given either subcutaneously or intramuscularly. Consider higher doses if the mother has been receiving oral anticoagulants.

A failure to respond (shortening of the INR in 2 to 4 hours) may indicate another diagnosis or coagulation disorder.

2.4 Directions for Dilution

Dilute phytonadione injectable emulsion with 0.9% Sodium Chloride Injection, 5% Dextrose Injection, or 5% Dextrose and Sodium Chloride Injection. Avoid use of other diluents that may contain benzyl alcohol, which can cause serious toxicity in newborns or low birth weight infants [see Warnings and Precautions (5.2) and Use in Specific Populations (8.4)].

When diluted, start administration of phytonadione injectable emulsion immediately after dilution.

Discard unused portions of diluted solution as well as unused contents of the vial.

Protect phytonadione injectable emulsion from light at all times.

Parenteral drug products should be inspected visually for particulate matter and discoloration prior to administration, whenever solution and container permit.

3 DOSAGE FORMS AND STRENGTHS

Injection: 2 mg/mL and 10 mg/mL single-dose vials.

4 CONTRAINDICATIONS

Hypersensitivity to phytonadione or any other component of this medication [see Warnings and Precautions (5.1)].

5 WARNINGS AND PRECAUTIONS

5.1 Hypersensitivity Reactions

Fatal and severe hypersensitivity reactions, including anaphylaxis, have occurred with intravenous or intramuscular administration of phytonadione injectable emulsion. Reactions have occurred despite dilution to avoid rapid intravenous infusion and upon first dose. These reactions have included shock, cardiorespiratory arrest, flushing, diaphoresis, chest pain, tachycardia, cyanosis, weakness, and dyspnea. Administer phytonadione injectable emulsion subcutaneously whenever feasible. Avoid the intravenous and intramuscular routes of administration unless the subcutaneous route is not feasible and the serious risk is justified [see Dosage and Administration (2.1)].

5.2 Risk of Serious Adverse Reaction in Infants due to Benzyl Alcohol Preservative

Use benzyl alcohol-free formulations in neonates and infants, if available. Serious and fatal adverse reactions including "gasping syndrome" can occur in neonates and infants treated with benzyl alcohol-preserved drugs, including phytonadione injectable emulsion. The "gasping syndrome" is characterized by central nervous system depression, metabolic acidosis, and gasping respirations.

When prescribing phytonadione injectable emulsion in infants, consider the combined daily metabolic load of benzyl alcohol from all sources including phytonadione injectable emulsion (contains 9 mg of benzyl alcohol per mL) and other drugs containing benzyl alcohol. The minimum amount of benzyl alcohol at which serious adverse reactions may occur is not known [see Use in Specific Populations (8.1, 8.2 and 8.4)].

5.3 Cutaneous Reactions

Parenteral administration of vitamin K replacements (including phytonadione injectable emulsion) may cause cutaneous reactions. Reactions have included eczematous reactions, scleroderma-like patches, urticaria, and delayed-type hypersensitivity reactions. Time of onset ranged from 1 day to a year after parenteral administration. Discontinue phytonadione injectable emulsion for skin reactions and institute medical management.

6 ADVERSE REACTIONS

The following serious adverse reactions are described elsewhere in the labeling:

- Hypersensitivity Reactions [see Warnings and Precautions (5.1)]
- Cutaneous Reactions [see Warnings and Precautions (5.3)]

6.1 Clinical Trials and Post-Marketing Experience

Because clinical trials are conducted under widely varying conditions, adverse reaction rates observed in the clinical trials of a drug cannot be directly compared to rates in the clinical trials of another drug and may not reflect the rates observed in practice.

The following adverse reactions have been identified during post-approval use of phytonadione injectable emulsion. Because these reactions were reported voluntarily from a population of uncertain size, it is not always possible to reliably estimate their frequency or establish a causal relationship to drug exposure.

Cardiac Disorders: Tachycardia, hypotension.

General disorders and administration site conditions: Generalized flushing; pain, swelling, and tenderness at injection site.

Hepatobiliary Disorders: Hyperbilirubinemia

Immune System Disorders: Fatal hypersensitivity reactions, anaphylactic reactions.

Neurologic: Dysgeusia, dizziness.

Pulmonary: Dyspnea.

Skin and Subcutaneous Tissue Disorders: Erythema, pruritic plaques, scleroderma-like lesions, erythema perstans.

Vascular: Cyanosis.

7 DRUG INTERACTIONS

Anticoagulants

Phytonadione injectable emulsion may induce temporary resistance to prothrombin-depressing anticoagulants, especially when larger doses of phytonadione injectable emulsion are used. Should this occur, higher doses of anticoagulant therapy may be needed when resuming anticoagulant therapy, or a change in therapy to a different class of anticoagulant may be necessary (i.e., heparin sodium).

Phytonadione injectable emulsion does not affect the anticoagulant action of heparin.

8 USE IN SPECIFIC POPULATIONS

8.1 Pregnancy

Risk Summary

Phytonadione injectable emulsion contains benzyl alcohol, which has been associated with gasping syndrome in neonates. The preservative benzyl alcohol can cause serious adverse events and death when administered intravenously to neonates and infants. If phytonadione injectable emulsion is needed during pregnancy, consider using a benzyl alcohol-free formulation [see Warnings and Precautions (5.2), Use in Specific Populations (8.4)].

Published studies with the use of phytonadione during pregnancy have not reported a clear association with phytonadione and adverse developmental outcomes [see Data]. There are maternal and fetal risks associated with vitamin K deficiency during pregnancy [see Clinical Considerations]. Animal reproduction studies have not been conducted with phytonadione.

The estimated background risk for the indicated population is unknown. All pregnancies have a background risk of birth defect, loss, or other adverse outcomes. In the U.S. general population, the estimated background risk of major birth defects and miscarriage in clinically recognized pregnancies is 2-4% and 15-20%, respectively.

Clinical Considerations

Disease-associated maternal and/or embryo/fetal risk

Pregnant women with vitamin K deficiency hypoprothrombinemia may be at an increased risk for bleeding diatheses during pregnancy and hemorrhagic events at delivery. Subclinical maternal vitamin K deficiency during pregnancy has been implicated in rare cases of fetal intracranial hemorrhage.

Data

Human Data

Phytonadione has been measured in cord blood of infants whose mothers were treated with phytonadione during pregnancy in concentrations lower than seen in maternal plasma. Administration of vitamin K1 to pregnant women shortly before delivery increased both maternal and cord blood concentrations. Published data do not report a clear association with phytonadione and adverse maternal or fetal outcomes when used during pregnancy. However, these studies cannot definitively establish the absence of any risk because of methodologic limitations including small sample size and lack of blinding.

Animal Data

In pregnant rats receiving vitamin K1 orally, fetal plasma and liver concentrations increased following administration, supporting placental transfer.

8.2 Lactation

Risk Summary

Phytonadione injectable emulsion contains benzyl alcohol. If available, preservative-free phytonadione injectable emulsion is recommended when phytonadione injectable emulsion is needed during lactation [see Warnings and Precautions (5.2), Use in Specific Populations (8.4)].

Phytonadione is present in breastmilk. There are no data on the effects of phytonadione injectable emulsion on the breastfed child or on milk production. The developmental and health benefits of breastfeeding should be considered along with the clinical need for phytonadione injectable emulsion and any potential adverse effects on the breastfed child from phytonadione injectable emulsion or from the underlying maternal condition.

8.4 Pediatric Use

The safety and effectiveness of phytonadione injectable emulsion for prophylaxis and treatment of vitamin K deficiency have been established in neonates. Use of phytonadione injection for prophylaxis and treatment of vitamin K deficiency is based on published clinical studies.

Serious adverse reactions including fatal reactions and the "gasping syndrome" occurred in premature neonates and infants in the intensive care unit who received drugs containing benzyl alcohol as a preservative. In these cases, benzyl alcohol dosages of 99 to 234 mg/kg/day produced high levels of benzyl alcohol and its metabolites in the blood and urine (blood levels of benzyl alcohol were 0.61 to 1.378 mmol/L). Additional adverse reactions included gradual neurological deterioration, seizures, intracranial hemorrhage, hematologic abnormalities, skin breakdown, hepatic and renal failure, hypotension, bradycardia, and cardiovascular collapse. Preterm, low-birth weight infants may be more likely to develop these reactions because they may be less able to metabolize benzyl alcohol.

When prescribing phytonadione injectable emulsion in infants consider the combined daily metabolic load of benzyl alcohol from all sources including phytonadione injectable emulsion (phytonadione injectable emulsion contains 9 mg of benzyl alcohol per mL) and other drugs containing benzyl alcohol. The minimum amount of benzyl alcohol at which serious adverse reactions may occur is not known [see Warnings and Precautions (5.2)].

Whenever possible, use preservative-free phytonadione formulations in neonates. The preservative benzyl alcohol has been associated with serious adverse events and death in pediatric patients. Premature and low-birth weight infants may be more likely to develop toxicity.

10 OVERDOSAGE

Hemolysis, jaundice, and hyperbilirubinemia in newborns, particularly in premature infants, may result from phytonadione injectable emulsion overdose.

11 DESCRIPTION

Phytonadione is a vitamin K replacement, which is a clear, yellow to amber, viscous, odorless or nearly odorless liquid. It is insoluble in water, soluble in chloroform and slightly soluble in ethanol. It has a molecular weight of 450.70.

Phytonadione is 2-methyl-3-phytyl-1, 4-naphthoquinone. Its empirical formula is C31H46O2 and its molecular structure is:

Phytonadione injectable emulsion, USP is a clear yellow, sterile, aqueous colloidal solution of vitamin K1, with a pH of 4.5 to 7.0, available for injection by the intravenous, intramuscular, and subcutaneous routes. Phytonadione injectable emulsion, USP is available in 1 mg (2 mg/mL) and 10 mg (10 mg/mL) single-dose vials. Each milliliter of phytonadione injectable emulsion, USP contains the following inactive ingredients: 70 mg polyoxyl 35 castor oil, 37.5 mg dextrose monohydrate, 9 mg benzyl alcohol (preservative), and water for injection. Phytonadione injectable emulsion, USP contains glacial acetic acid for pH adjustment to 6.3 (4.5 – 7.0).

12 CLINICAL PHARMACOLOGY

12.1 Mechanism of Action

Phytonadione injectable emulsion aqueous colloidal solution of vitamin K1 for parenteral injection, possesses the same type and degree of activity as does naturally-occurring vitamin K, which is necessary for the production via the liver of active prothrombin (factor II), proconvertin (factor VII), plasma thromboplastin component (factor IX), and Stuart factor (factor X). Vitamin K is an essential cofactor for a microsomal enzyme that catalyzes the post- translational carboxylation of multiple, specific, peptide-bound glutamic acid residues in inactive hepatic precursors of factors II, VII, IX, and X. The resulting gamma-carboxy-glutamic acid residues convert the precursors into active coagulation factors that are subsequently secreted by liver cells into the blood.

In normal animals and humans, phytonadione is virtually devoid of activity. However, in animals and humans deficient in vitamin K, the pharmacological action of vitamin K is related to its normal physiological function, that is, to promote the hepatic biosynthesis of vitamin K dependent clotting factors.

12.2 Pharmacodynamics

The action of the aqueous dispersion, when administered intravenously, is generally detectable within an hour or two and hemorrhage is usually controlled within 3 to 6 hours. A normal INR may often be obtained in 12 to 14 hours.

12.3 Pharmacokinetics

Absorption:

Phytonadione is readily absorbed following intramuscular administration.

Distribution:

After absorption, phytonadione is initially concentrated in the liver, but the concentration declines rapidly. Very little vitamin K accumulates in tissues.

Elimination:

Little is known about the metabolic fate of vitamin K. Almost no free unmetabolized vitamin K appears in bile or urine.

13 NONCLINICAL TOXICOLOGY

13.1 Carcinogenesis, Mutagenesis, Impairment of Fertility

Studies of carcinogenicity, genotoxicity or impairment of fertility have not been conducted with phytonadione.

16 HOW SUPPLIED/STORAGE AND HANDLING

Phytonadione injectable emulsion, USP is a clear yellow, sterile, aqueous colloidal solution and is supplied in a package of 10 as follows:

NDC No. | Container | Amount of Phytonadione injectable emulsion In Container | Volume | Concentration
69097-709-96 | 10 single-dose vials per carton | 1 mg | 0.5 mL | 2 mg/mL
69097-708-96 | 10 single-dose vials per carton | 10 mg | 1 mL | 10 mg/mL

Store at 20° to 25°C (68° to 77°F); [see USP Controlled Room Temperature].

Protect phytonadione injectable emulsion from light. Store container in closed original carton until contents have been used.

17 PATIENT COUNSELING INFORMATION

Inform the patient of the following important risks of phytonadione injectable emulsion:

Serious Hypersensitivity Reactions

Advise the patient and caregivers to immediately report signs of hypersensitivity after receiving phytonadione injectable emulsion [see Warnings and Precautions (5.1)].

Risk of Gasping Syndrome Due to Benzyl Alcohol

Advise the patient and caregivers of the risk of gasping syndrome associated with the use of products that contain benzyl alcohol (including phytonadione injectable emulsion) in neonates, infants, and pregnant women [see Warnings and Precautions (5.2)].

Cutaneous Reactions

Advise the patient and caregivers to report the occurrence of new rashes after receiving phytonadione injectable emulsion. These reactions may be delayed for up to a year after treatment [see Warnings and Precautions (5.3)].

Manufactured by: Cipla Ltd., India

At M/s Immacule Lifesciences Pvt. Ltd. India

Manufactured for:

Cipla USA, Inc.

10 Independence Boulevard, Suite 300,

Warren, NJ 07059

Revised: 3 /2022

PACKAGE LABEL.PRINCIPAL DISPLAY PANEL

NDC 69097-709-30 RX Only

Phytonadione

Injectable Emulsion, USP

1 mg/0.5 mL

Neonatal Concentration

0.5 mL Single-Dose Vial

Contains no more

than 500 mcg/L

of aluminum.

Protect from Light.

Cipla

NDC 69097-708-31 RX Only

Phytonadione

Injectable Emulsion, USP10 mg/ mL

1 mL Single-Dose Vial

Contains no more than

500 mcg/L of aluminum.

Protect from Light.

Cipla

NDC 69097-709-96 RX Only

Phytonadione

Injectable Emulsion, USP

1 mg/0.5 mL

Neonatal Concentration

For INTRAMUSCULAR, SUBCUTANEOUS or

INTRAVENOUS (with caution).

Protect from light.

Keep vials in carton until time of use.

10 X 0.5 mL vials per carton

Single-Dose Vials

Cipla

NDC 69097-708-96 RX Only

Phytonadione

Injectable Emulsion, USP

10 mg/ mL

For INTRAMUSCULAR, SUBCUTANEOUS or

INTRAVENOUS (with caution).

Protect from light.

Keep vials in carton until time of use.

10 X 1 mL vials per carton

Single-Dose Vials

Cipla